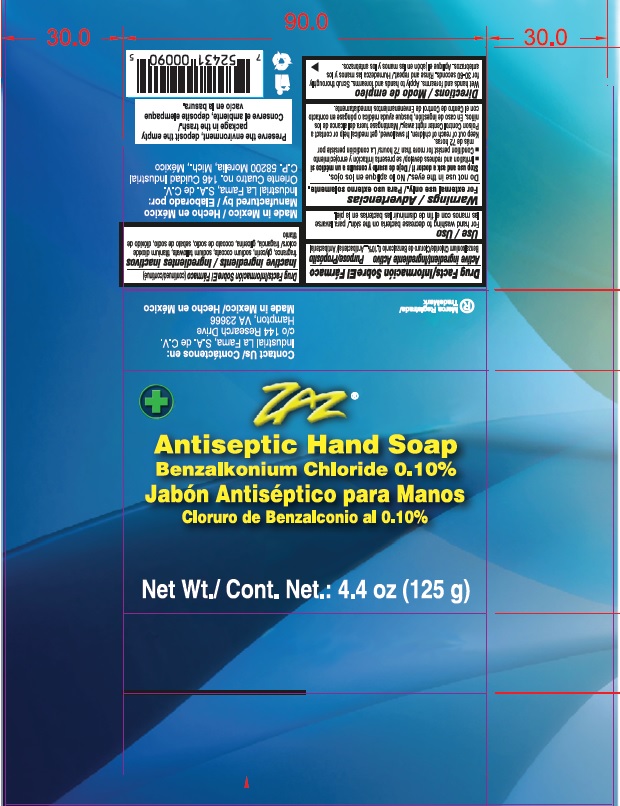 DRUG LABEL: ZAZ Antiseptic Hand
NDC: 82726-001 | Form: SOAP
Manufacturer: INDUSTRIAL LA FAMA SA DE CV
Category: otc | Type: HUMAN OTC DRUG LABEL
Date: 20220509

ACTIVE INGREDIENTS: BENZALKONIUM CHLORIDE 0.1 g/100 g
INACTIVE INGREDIENTS: SODIUM COCOATE; GLYCERIN; TITANIUM DIOXIDE; WATER; SODIUM TALLOWATE, BEEF

Active ingredient

Benzalkonium chloride 0.1%

Purpose

Antibacterial

Uses

For hand washing to decrease bacteria on the skin

Warnings

For external use only

Do not use in eyes

Stop use and ask a doctor if

- Irritation and redness develop

- Condition persist for more than 72 hours

Keep out of reach of children If swallowed, get medical help or contact a Poison Control Center right away

Direction

Wet hands and forearms. Apply to hands and forearms. Scrub thoroughly for 30-60 seconds. Rinse and repeat.

Inactive ingredients

Fragrance, gliceryn, sodium cocoate, sodium tallowate, titanium dioxide, colors.